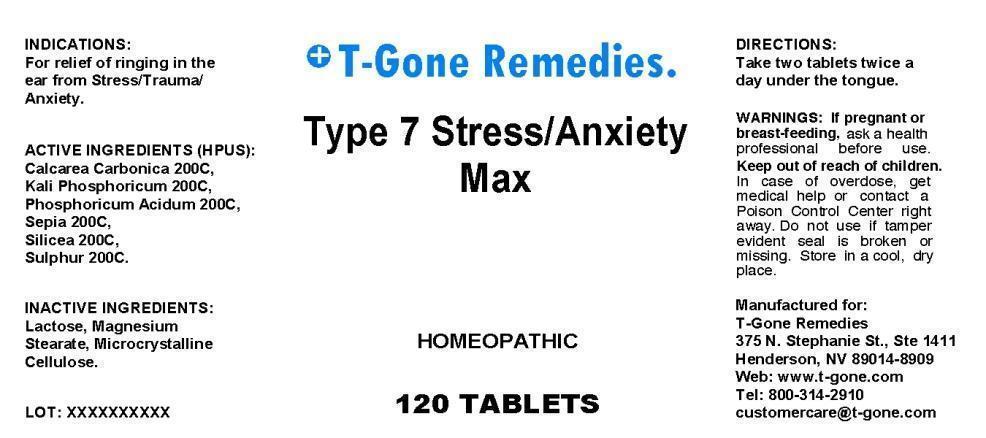 DRUG LABEL: Type 7 Stress Anxiety Max
NDC: 50169-0007 | Form: TABLET
Manufacturer: TGone Remedies Ltd
Category: homeopathic | Type: HUMAN OTC DRUG LABEL
Date: 20140708

ACTIVE INGREDIENTS: OYSTER SHELL CALCIUM CARBONATE, CRUDE 200 [hp_C]/1 mg; POTASSIUM PHOSPHATE, DIBASIC 200 [hp_C]/1 mg; PHOSPHORIC ACID 200 [hp_C]/1 mg; SEPIA OFFICINALIS JUICE 200 [hp_C]/1 mg; SILICON DIOXIDE 200 [hp_C]/1 mg; SULFUR 200 [hp_C]/1 mg
INACTIVE INGREDIENTS: LACTOSE; MAGNESIUM STEARATE; CELLULOSE, MICROCRYSTALLINE

DRUG FACTS

ACTIVE INGREDIENTS:

Calcarea Carbonica 200C, Kali Phosphoricum 200C, Phosphoricum Acidum 200C, Sepia 200C, Silicea 200C, Sulphur 200C

INDICATIONS:

For relief of ringing in the ear from Stress Trauma Anxiety.

WARNINGS:

If pregnant or breast-feeding, ask a health professional before use.

Keep out of reach of children. In case of overdose, get medical help or contact a Poison Control Center right away.

Do not use if tamper evident seal is broken or missing.

Store in a cool, dry place.

KEEP OUT OF THE REACH OF CHILDREN:

Keep out of reach of children. In case of overdose, get medical help or contact a Poison Control Center right away.

DIRECTIONS:

Take two tablets twice a day under the tongue.

INDICATIONS:

For relief of ringing in the ear from Stress Trauma Anxiety.

INACTIVE INGREDIENTS:

Lactose, Magnesium Stearate, Microcrystalline Cellulose.

QUESTIONS:

Manufactured for:

T-Gone Remedies

375 N. Stephanie St., Ste 1411

Henderson, NV 89014-8909

Web: www.t-gone.com

Tel: 800-314-2910

customercare@t-gone.com

PACKAGE LABEL DISPLAY:

T-Gone Remedies.

Type 7 Stress Anxiety Max

HOMEOPATHIC

120 TABLETS